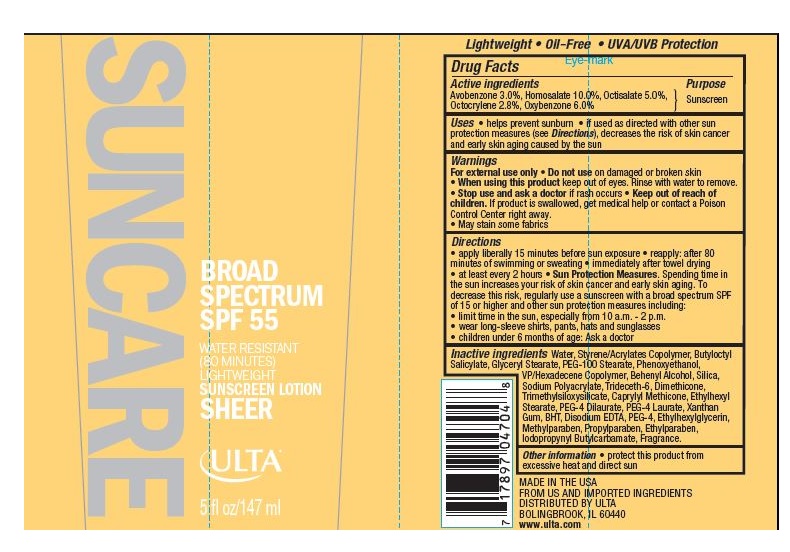 DRUG LABEL: ULTA SUN DRY TOUCH SPF 55
                        
NDC: 62296-7866 | Form: LOTION
Manufacturer: Ulta
Category: otc | Type: HUMAN OTC DRUG LABEL
Date: 20160519

ACTIVE INGREDIENTS: AVOBENZONE 3 g/100 g; HOMOSALATE 10 g/100 g; OCTISALATE 5 g/100 g; OCTOCRYLENE 2 g/100 g; OXYBENZONE 6 g/100 g
INACTIVE INGREDIENTS: Water; BUTYLOCTYL SALICYLATE; GLYCERYL MONOSTEARATE; PEG-100 STEARATE; PHENOXYETHANOL; VINYLPYRROLIDONE/HEXADECENE COPOLYMER; DOCOSANOL; SILICON DIOXIDE; TRIDECETH-6; DIMETHICONE; CAPRYLYL TRISILOXANE; ETHYLHEXYL STEARATE; PEG-4 DILAURATE; PEG-4 LAURATE; XANTHAN GUM; BUTYLATED HYDROXYTOLUENE; EDETATE DISODIUM; POLYETHYLENE GLYCOL 200; ETHYLHEXYLGLYCERIN; METHYLPARABEN; PROPYLPARABEN; ETHYLPARABEN; IODOPROPYNYL BUTYLCARBAMATE

Drug Facts

Active Ingredients

AVOBENZONE 3.0%, HOMOSALATE 10.0%, OCTISALATE 5.0%, OCTOCRYLENE 2.8%,

OXYBENZONE 6.0%

Purpose

Suncreen

Uses

- helps prevent sunburn
- if used as directed with other sun protection measures (see Directions),decreases the risk of skin cancer and early skin aging caused by the sun

Warnings

For external use only

Do not use

on damaged or broken skin

When using this product

keep out of eyes. Rinse with water to remove.

Stop use and ask a doctor

if rash occurs

Keep out of reach of children.

If product is swallowed, get medical help or contact a Poison Control Center right away.

- May stain some fabrics

Directions

- apply liberally 15 minutes before sun exposure
- reapply: after 80 minutes of swimming or sweating
- Immediately after towel drying
- at least every 2 hours
- Sun Protection Measures: Spending time in the sun increases your risk of skin cancer and early skin aging. To decrease this risk, regularly use a sunscreen with a broad spectrum SPF of 15 or higher and other sun protection measures including:
- limit time in the sun, especially from 10 a.m. - 2 p.m.
- wear long-sleeve shirts, pants, hats and sunglasses
- children under 6 months of age: Ask a doctor

Inactive Ingredients

Water, Styrene/Acrylates Copolymer, Butyloctyl Salicylate, Glyceryl Stearate, PEG-100, Stearate, Phenoxyethanol, VP/Hexadecene Copolymer, Behenyl Alcohol, Silica, Trideceth-6, Sodium Polyacrylate, Dimethicone, Methylparaben, Trimethylsiloxysilicate, Fragrance, Caprylyl Methicone, Ethylhexyl Stearate, Propylparaben, PEG-4 Dilaurate, PEG-4 Laurate, BHT, Disodium EDTA, Ethylparaben, Xanthan Gum, Iodopropynyl Butylcarbamate, PEG-4, Ethylhexylglycerin.

Other information:

- protect this product from excessive heat and direct sun

Principle Display Panel

62296-7866-4
SUNCARE
BROAD SPECTRUM
SPF 55

WATER RESISTANT

(80 MINUTES)

LIGHTWEIGHT

SUNSCREEN LOTION
SHEER

ULTA

5 fl oz/147 ml